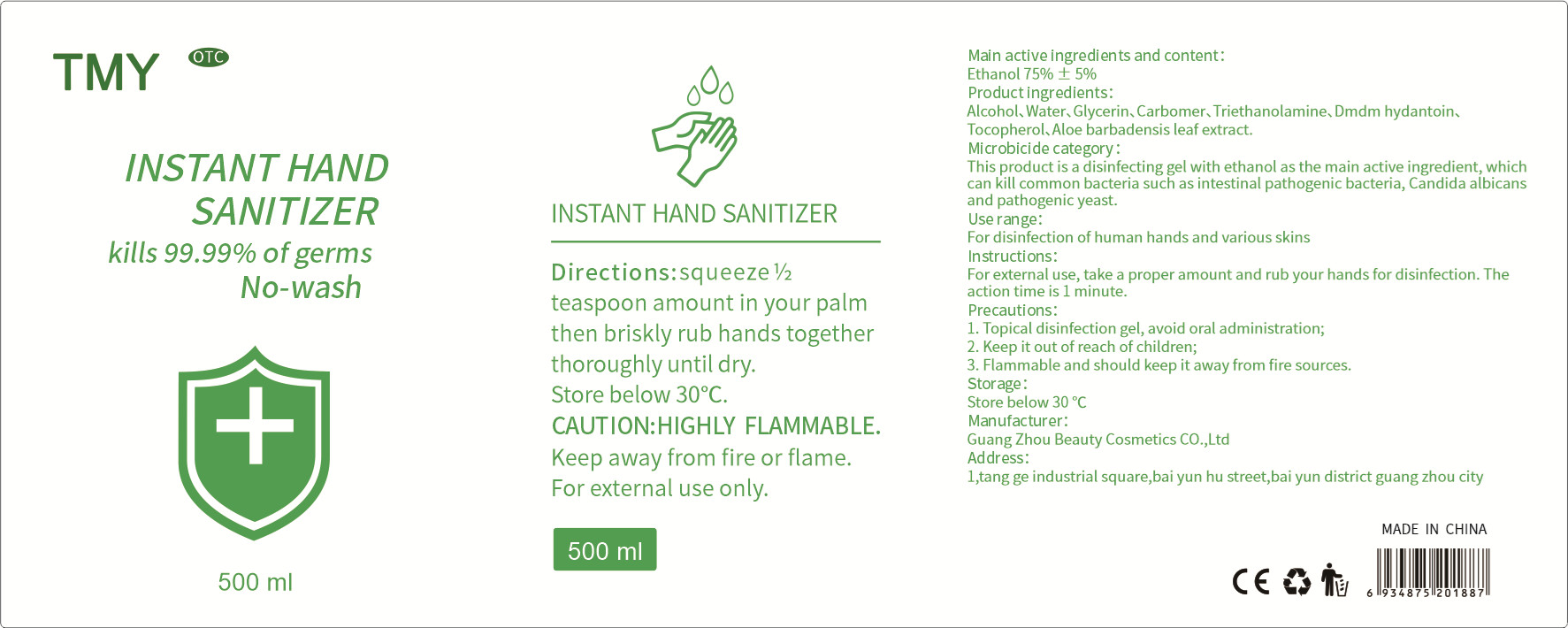 DRUG LABEL: INSTANT HAND SANITIZER
NDC: 40303-006 | Form: GEL
Manufacturer: Guangzhou Beauty Cosmetics Co., Ltd.
Category: otc | Type: HUMAN OTC DRUG LABEL
Date: 20200421

ACTIVE INGREDIENTS: ALCOHOL 375 mL/500 mL
INACTIVE INGREDIENTS: TROLAMINE; DMDM HYDANTOIN; GLYCERIN; CARBOMER COPOLYMER TYPE A (ALLYL PENTAERYTHRITOL CROSSLINKED); ALOE VERA LEAF; TOCOPHEROL; WATER

DOSAGE AND ADMINISTRATION

Store below 30 °C

INACTIVE INGREDIENT

Water

Glycerin

Carbomer

Triethanolamine

Dmdm hydantoin

Tocopherol

Aloe barbadensis leaf extract

INDICATIONS AND USAGE

For external use, take a proper amount and rub your hands for disinfection. The action time is 1 minute.

ACTIVE INGREDIENT

Alcohol

keep out of children

PURPOSE

Disinfection
Sterilization
No Rinseing

WARNINGS

1. Topical disinfection gel, avoid oral administration;
2. Keep it out of reach of children;
3. Flammable and should keep it away from fire sources.